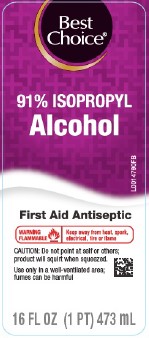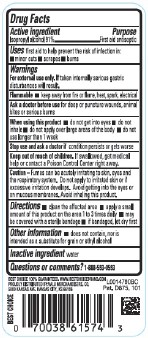 DRUG LABEL: Isopropyl Alcohol
NDC: 63941-804 | Form: LIQUID
Manufacturer: Valu Merchandisers Company
Category: otc | Type: HUMAN OTC DRUG LABEL
Date: 20260216

ACTIVE INGREDIENTS: ISOPROPYL ALCOHOL 91 mL/100 mL
INACTIVE INGREDIENTS: WATER

Best Choice 804.003/804AA
91% Isopropyl Alcohol

Active Ingredient

Isopropyl alcohol 91%

Purpose

First aid antiseptic

Uses

helps prevent the risk of infection in:

- minor cuts
- scrapes
- burns

Warnings

For external use only. If taken interally serious gastric disurbnces will result.

Flammable

- Keep away from fire or flame, heat, spark, electrical

Ask a doctor before use

for deep or puncture wounds, animal bites or serious burns

When using this product

- do not get into eyes
- do not inhale
- do not apply over large areas of the body
- do not use longer than 1 week

Stop use and ask a doctor if

condition persists or gets worse

Keep out of reach of children.

If swallowed, get medical help or contact a Poison Control Center right away.

Caution

Fumes can be acutely irritating to skin, eyes and respiratory system. Do not apply to irritated skin or if excessive irritation develops. Avoid getting into the eyes or on mucous membranes. Avoid inhaling this product.

Directions

- clean the affected area
- apply a small amount of this product on the area 1 to 3 times daily
- may be covered with a sterile bandage
- if bandaged, let dry first

other information

- does not contain, nor is intended as a substitute for grain or ethyl alcohol

Inactive ingredient

water

Questions or comments?

1-888-593-0593

ADVERSE REACTION

BEST CHOICE 100% GUARANTEED. WWW.BESTCHOICEBRAND.COM

PROUDLY DISTRIBUTED BY: VALU MERCHANDISERS, CO

5000 KANSAS AVE. KANSAS CITY, KS 66106

Pat. D675,101

principal display panel

Best Choice®

91% ISOPROPYL Alcohol

First Aid Antiseptic

WARNING FLAMMABLE - Kep away from heat, spark, electrical, fire or flame

CAUTION: Do not point at self or others; product will squirt when squeezed.

Use only in a well-ventilated area; fumes can be harmful

16 FL OZ (1 PT) 473 mL